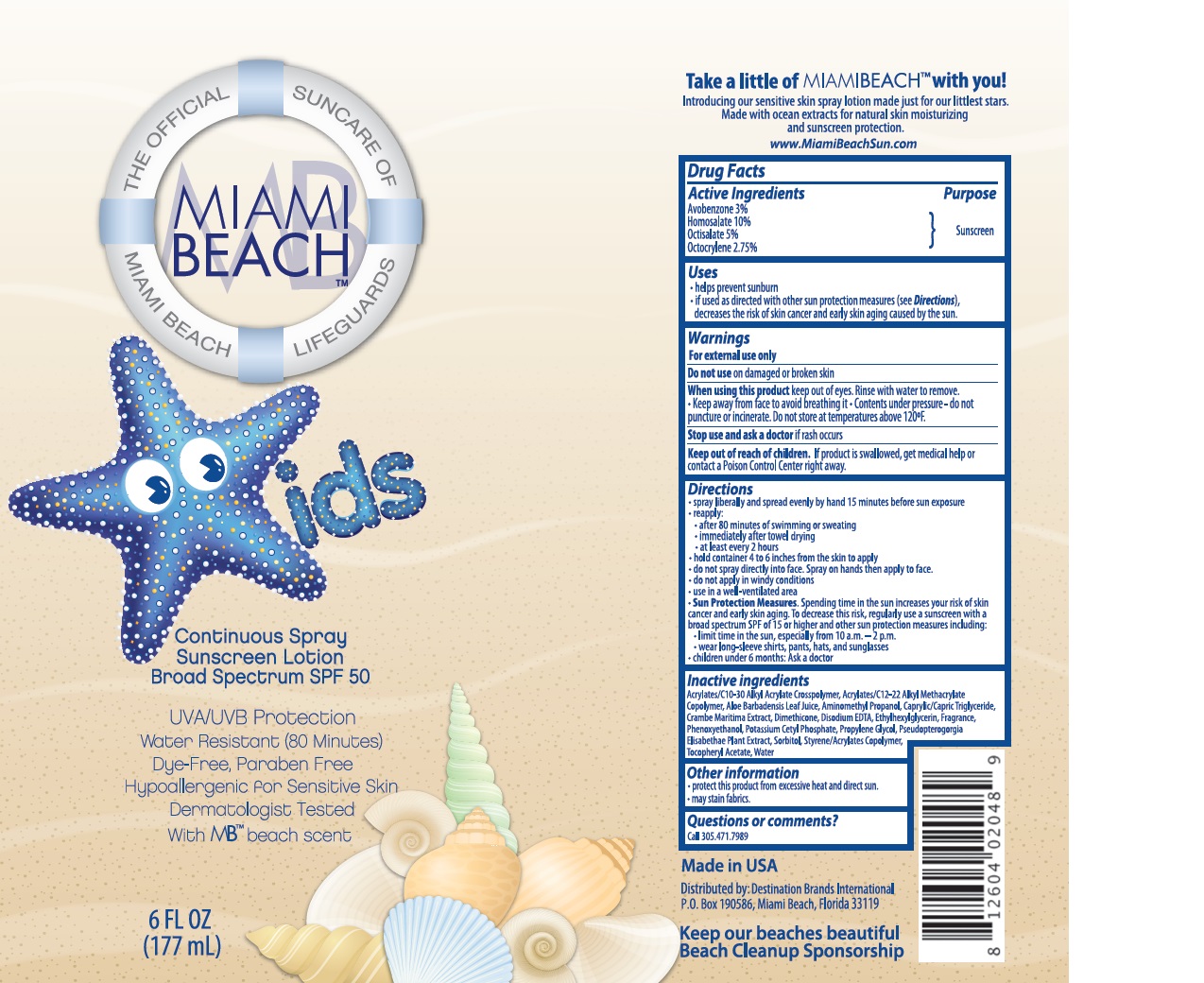 DRUG LABEL: Miami Beach
NDC: 13630-0104 | Form: SPRAY
Manufacturer: Prime Packaging Inc.
Category: otc | Type: HUMAN OTC DRUG LABEL
Date: 20200117

ACTIVE INGREDIENTS: AVOBENZONE 30.66 mg/1 mL; HOMOSALATE 102.2 mg/1 mL; OCTISALATE 51.1 mg/1 mL; OCTOCRYLENE 28.11 mg/1 mL
INACTIVE INGREDIENTS: STYRENE/ACRYLAMIDE COPOLYMER (MW 500000); BUTYL ACRYLATE/C16-C20 ALKYL METHACRYLATE/METHACRYLIC ACID/METHYL METHACRYLATE COPOLYMER; POTASSIUM CETYL PHOSPHATE; DIMETHICONE; CRAMBE MARITIMA LEAF; MEDIUM-CHAIN TRIGLYCERIDES; ETHYLHEXYLGLYCERIN; CARBOMER COPOLYMER TYPE A (ALLYL PENTAERYTHRITOL CROSSLINKED); ALOE VERA LEAF; SORBITOL; PROPYLENE GLYCOL; EDETATE DISODIUM; AMINOMETHYLPROPANOL; PSEUDOPTEROGORGIA ELISABETHAE; .ALPHA.-TOCOPHEROL ACETATE; WATER; PHENOXYETHANOL

Miami Beach SPF 50 Kids C/S Sunscreen

Active Ingredients

Avobenzone 3%

Homosalate 10%

Octisalate 5%

Octocrylene 2.75%

Purpose

Sunscreen

Uses

- helps prevent sunburn
- if used as directed with other sun protection measures (see Directions), decreases the risk of skin cancer and early skin aging caused by the sun.

Warnings

For external use only

Do not use on damaged or broken skin

When using this product keep out of eyes. Rinse with water to remove.

- keep away from face to avoid breathing it
- Contents under pressure - do not puncture or incinerate. Do not store at temperatures above 120°F

Stop use and ask a doctor if rash occurs

Keep out of reach of children. If product is swallowed, get medical help or contact a Poison Control Center right away.

Directions

- spray liberally and spread evenly by hand 15 minutes before sun exposure
- reapply:
- after 80 minutes of swimming and sweating
- immediately after towel drying
- at least every 2 hours
- hold container 4 to 6 inches from the skin to apply
- do not spray directly into face. Spray on hands then apply to face
- do not apply in windy conditions
- use in a well-ventilated area
- Sun Protection Measures. Spending time in the sun increases your risk of skin cancer and early skin aging. To decrease this risk, regularly use a sunscreen with a broad spectrum SPF of 15 or higher and other sun protection measures including:
- limit time in the sun, especially from 10 a. m. - 2 p. m.
- wear long-sleeve shirts, pants, hats, and sunglasses
- children under 6 months: Ask a doctor

INACTIVE INGREDIENT

Water (Aqua), Styrene/Acrylates Copolymer, Homosalate, Ethylhexyl Salicylate, Butyl Methoxydibenzoylmethane, Sorbitol, Octocrylene, Dimethicone, Acrylates/C12-22 Alkyl Methacrylate Copolymer, Phenoxyethanol, Potassium Cetyl Phosphate, Fragrance (Parfum), Acrylates/C10-30 Alkyl Acrylate Crosspolymer, Ethylhexylglycerin, Disodium EDTA, Tocopheryl Acetate, Butylphenyl Methylpropional, Aminomethyl Propanol, Aloe Barbadensis Leaf Juice, Hexyl Cinnamal, Linalool, Geraniol, Alpha-Isomethyl Ionone, Caprylic/Capric Triglyceride, Benzyl Salicylate, Propylene Glycol, Hydroxycitronellal, Limonene, Crambe Maritima Extract, Pseudopterogorgia Elisabethae Plant Extract

Other Information

- protect this product from excessive heat and direct sun
- may stain fabrics

Question or comments?

Call 305.471.7989